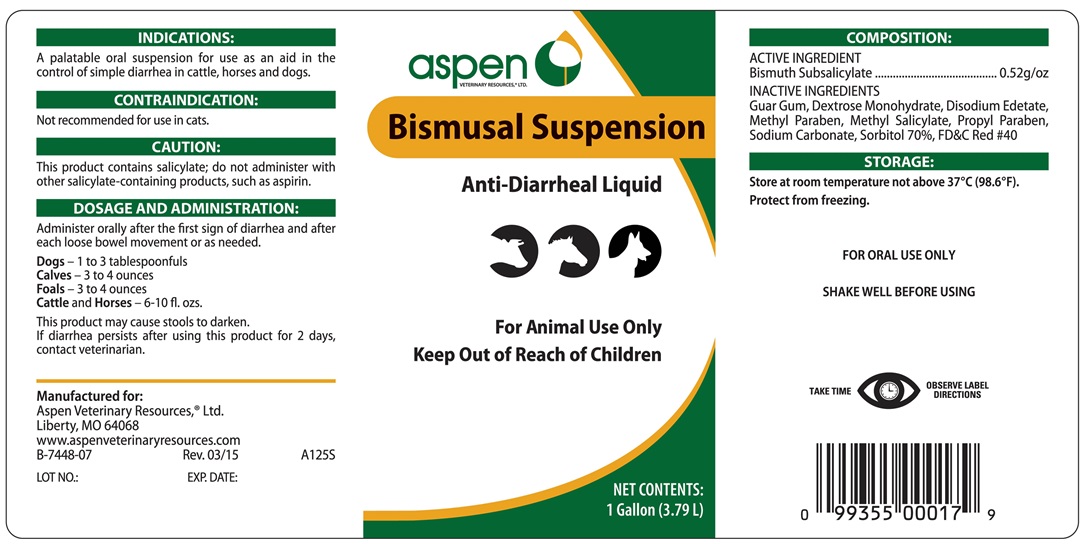 DRUG LABEL: BISMUSAL
                        
                        
                        
NDC: 46066-244 | Form: SUSPENSION
Manufacturer: Aspen Veterinary Resources, Ltd.
Category: animal | Type: OTC ANIMAL DRUG LABEL
Date: 20171011

ACTIVE INGREDIENTS: BISMUTH SUBSALICYLATE 66.2 mg/3.785 L

BISMUSAL SUSPENSION

INDICATIONS AND USAGE

Anti-Diarrheal Liquid

For Animal Use Only

Keep Out of Reach of Children

INDICATIONS

A palatable oral suspension for use as an aid in the control of simple diarrhea in cattle, horses, and dogs.

CONTRAINDICATIONS

Not recommended for use in cats.

DOSAGE AND ADMINISTRATION

Administer orally after the first sign of diarrhea and after each loose bowel movement or as needed.

Dogs - 1 to 3 tablespoons

Calves - 3 to 4 ounces

Foals - 3 to 4 ounces

Cattle and Horses - 6-10 fl. oz.

This product may cause stools to darken. If diarrhea persists after using this product for 2 days, contact veterinarian.

COMPOSITION

ACTIVE INGREDIENT

Bismuth Subsalicylate .......................... 0.52 g/oz

INACTIVE INGREDIENTS

Guar Gum, Dextrose Monohydrate, Disodium Edetate, Methyl Paraben, Methyl Salicylate, Propyl Paraben, Sodium Carbonate, Sorbitol 70%, FD&C Red #40.

STORAGE AND HANDLING

Store at room temrpeature not above 37°C (98.6°F)

Protect from freezing.

FOR ORAL USE ONLY

SHAKE WELL BEFORE USING.

TAKE TIME OBSERVE LABEL DIRECTIONS